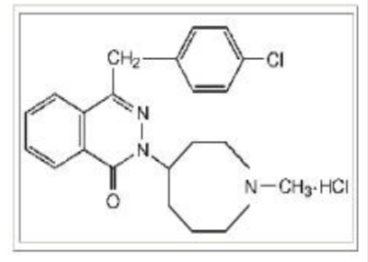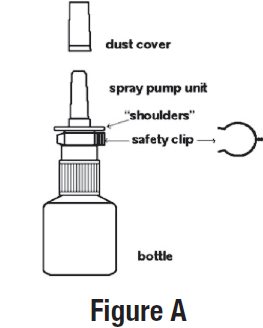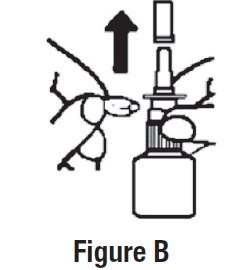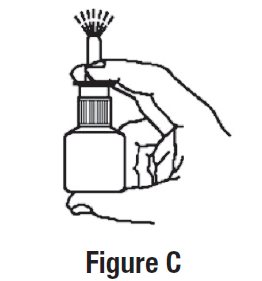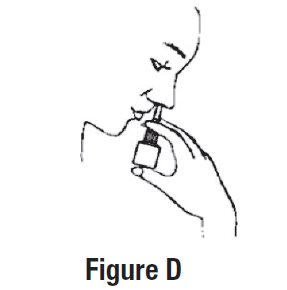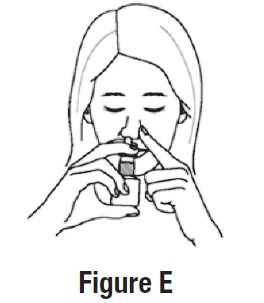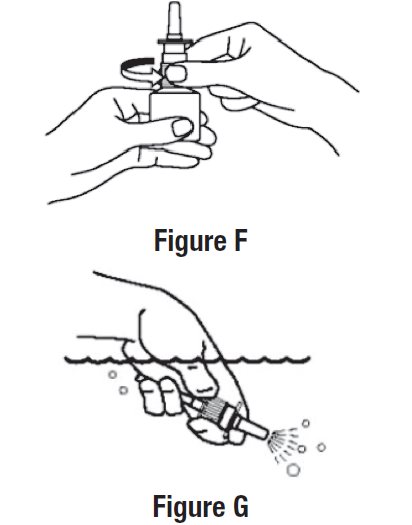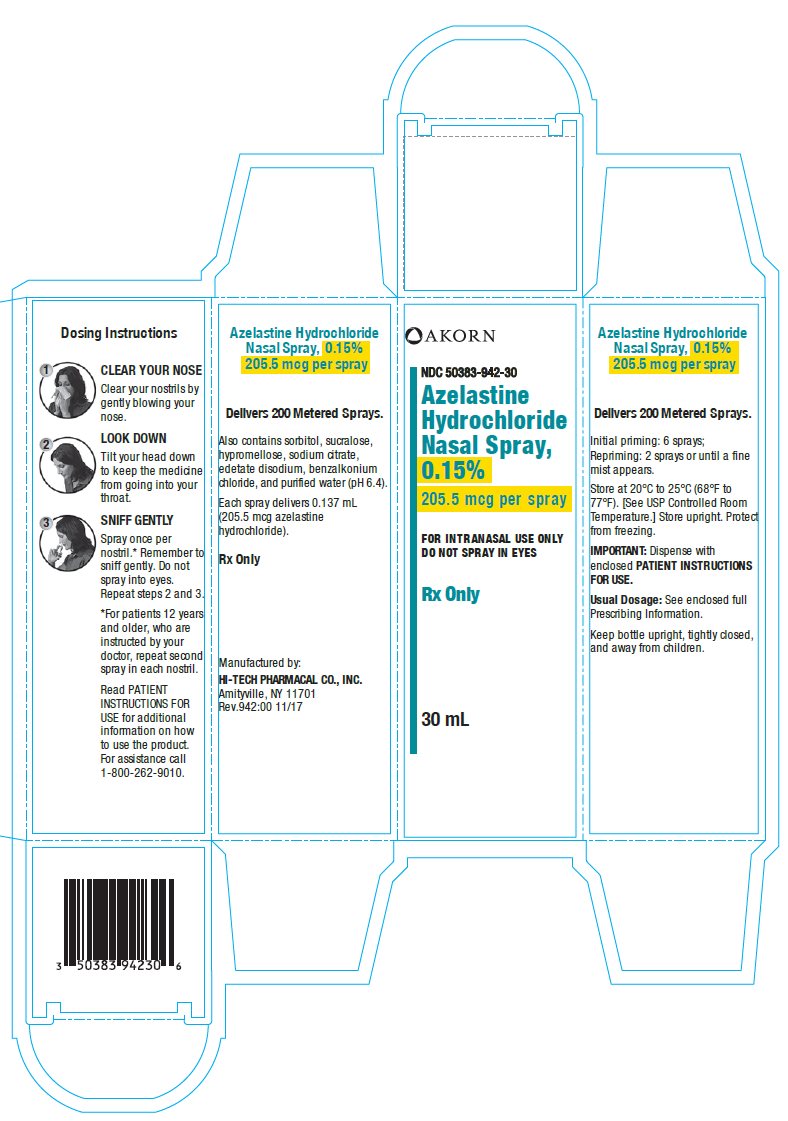 DRUG LABEL: Azelastine Hydrochloride
NDC: 50383-942 | Form: SPRAY, METERED
Manufacturer: Akorn
Category: prescription | Type: HUMAN PRESCRIPTION DRUG LABEL
Date: 20220301

ACTIVE INGREDIENTS: AZELASTINE HYDROCHLORIDE 1.5 mg/1 mL
INACTIVE INGREDIENTS: BENZALKONIUM CHLORIDE; EDETATE DISODIUM; HYPROMELLOSE, UNSPECIFIED; WATER; TRISODIUM CITRATE DIHYDRATE; SORBITOL; SUCRALOSE

HIGHLIGHTS OF PRESCRIBING INFORMATION

These highlights do not include all the information needed to use AZELASTINE HYDROCHLORIDE NASAL SPRAY safely and effectively. See full prescribing information for AZELASTINE HYDROCHLORIDE NASAL SPRAY.
AZELASTINE HYDROCHLORIDE nasal spray, for intranasal use
Initial U.S. Approval: 1996

1 INDICATIONS AND USAGE

Azelastine hydrochloride nasal spray is an H1-receptor antagonist indicated for the relief of the symptoms of:

- Seasonal allergic rhinitis in patients 6 years of age and older. (1.1)
- Perennial allergic rhinitis in patients 6 years of age and older. (1.1).

2 DOSAGE AND ADMINISTRATION

• For intranasal use only. (2.3)

• Seasonal allergic rhinitis:

- 6 to 11 years: Azelastine hydrochloride 0.15%: 1 spray per nostril twice daily. (2.1)
- Adults and adolescents 12 years of age and older:

○ Azelastine hydrochloride 0.15%: 1 or 2 sprays per nostril twice daily (2.1), or

○ 2 sprays per nostril once daily. (2.1)

• Perennial allergic rhinitis:

- 6 to 11 years: Azelastine hydrochloride 0.15%: 1 spray per nostril twice daily. (2.2)
- Adults and adolescents 12 years of age and older: Azelastine hydrochloride 0.15%: 2 sprays per nostril twice daily. (2.2)
- Prime azelastine hydrochloride nasal spray before initial use and when it has not been used for 3 or more days. (2.3)

3 DOSAGE FORMS AND STRENGTHS

Nasal spray solution available in one dosage strength:

- Azelastine hydrochloride nasal spray, 0.15%: 205.5 mcg of azelastine hydrochloride in each 0.137 mL spray. (3)

4 CONTRAINDICATIONS

None. (4)

5 WARNINGS AND PRECAUTIONS

- Somnolence: Avoid engaging in hazardous occupations requiring complete mental alertness such as driving or operating machinery when taking azelastine hydrochloride. (5.1)
- Avoid concurrent use of alcohol or other central nervous system (CNS) depressants with azelastine hydrochloride because further decreased alertness and impairment of CNS performance may occur. (5.1)

6 ADVERSE REACTIONS

The most common adverse reactions (≥2% incidence) are: pyrexia, dysgeusia, nasal discomfort, epistaxis, headache, sneezing, fatigue, somnolence, upper respiratory infection, cough, rhinalgia, vomiting, otitis media, contact dermatitis, and oropharyngeal pain. (6.1)

To report SUSPECTED ADVERSE REACTIONS, contact Hi-Tech Pharmacal Co., Inc. at 1-800-262-9010 or FDA at 1-800-FDA-1088 or www.fda.gov/medwatch.

FULL PRESCRIBING INFORMATION

1 INDICATIONS AND USAGE

1.1 Allergic Rhinitis

Azelastine hydrochloride nasal spray is indicated for the relief of the symptoms of seasonal allergic rhinitis in patients 6 years of age and older and perennial allergic rhinitis in patients 6 years of age and older.

2 DOSAGE AND ADMINISTRATION

2.1 Seasonal Allergic Rhinitis

Children 6 to 11 years of age: Azelastine hydrochloride nasal spray, 0.15%, 1 spray per nostril twice daily.

Adults and adolescents 12 years of age and older: Azelastine hydrochloride nasal spray, 0.15%, 1 or 2 sprays per nostril twice daily. Azelastine hydrochloride nasal spray 0.15% may also be administered as 2 sprays per nostril once daily.

2.2 Perennial Allergic Rhinitis

Children 6 to 11 years of age: Azelastine hydrochloride nasal spray, 0.15%, 1 spray per nostril twice daily.

Adults and adolescents 12 years of age and older: Azelastine hydrochloride nasal spray, 0.15%, 2 sprays per nostril twice daily.

2.3 Important Administration Instructions

Administer azelastine hydrochloride nasal spray by the intranasal route only.

Priming: Prime azelastine hydrochloride nasal spray before initial use by releasing 6 sprays or until a fine mist appears. When azelastine hydrochloride nasal spray has not been used for 3 or more days, reprime with 2 sprays or until a fine mist appears.

Avoid spraying azelastine hydrochloride nasal spray into the eyes.

3 DOSAGE FORMS AND STRENGTHS

Azelastine hydrochloride is a nasal solution:

Each spray of azelastine hydrochloride nasal spray, 0.15% delivers a volume of 0.137 mL solution containing 205.5 mcg of azelastine hydrochloride.

4 CONTRAINDICATIONS

None.

5 WARNINGS AND PRECAUTIONS

5.1 Activities Requiring Mental Alertness

In clinical trials, the occurrence of somnolence has been reported in some patients taking azelastine hydrochloride [see Adverse Reactions (6.1)]. Patients should be cautioned against engaging in hazardous occupations requiring complete mental alertness and motor coordination such as operating machinery or driving a motor vehicle after administration of azelastine hydrochloride. Concurrent use of azelastine hydrochloride with alcohol or other central nervous system depressants should be avoided because additional reductions in alertness and additional impairment of central nervous system performance may occur [see Drug Interactions (7.1)].

6 ADVERSE REACTIONS

Use of azelastine hydrochloride has been associated with somnolence [see Warnings and Precautions (5.1)].

6.1 Clinical Trials Experience

Because clinical trials are conducted under widely varying conditions, adverse reaction rates observed in clinical trials of a drug cannot be directly compared to rates in the clinical trials of another drug and may not reflect rates observed in practice.

Azelastine Hydrochloride Nasal Spray, 0.15%

The safety data described below reflect exposure to azelastine hydrochloride nasal spray, 0.15% in 2114 patients (6 months of age and older) with season or perennial allergic rhinitis from 10 clinical trials of 2 weeks to 12 months duration. In 8 double-blind, placebo-controlled clinical trials of 2 to 4 weeks duration, 1703 patients (646 males and 1059 females) with seasonal or perennial allergic rhinitis were treated with azelastine hydrochloride 0.15% one or two sprays per nostril once or twice daily. In the 12 month open-label, active-controlled clinical trial, 466 patients (156 males and 310 females) with perennial allergic rhinitis were treated with azelastine hydrochloride 0.15% two sprays per nostril twice daily. Of these 466 patients, 152 had participated in the 4-week placebo-controlled perennial allergic rhinitis clinical trials. In a 4-week, double-blind, placebo-controlled clinical trial, 161 patients (87 males and 74 females) ages 6 to 11 years of age with perennial allergic rhinitis, with or without concomitant seasonal allergic rhinitis, were treated with azelastine hydrochloride 0.15% one spray per nostril twice daily. In a 4-week clinical trial, 95 patients (59 males and 36 females) ages 6 months to 5 years of age with seasonal and/ or perennial allergic rhinitis were treated with azelastine hydrochloride 0.15% one spray per nostril twice daily. The racial distribution for the 10 clinical trials was 79% white, 14% black, 2% Asian, and 5% other.

Adults and Adolescents 12 Years of Age and Older

In the 7 placebo controlled clinical trials of 2 to 4 week duration, 2343 patients with seasonal allergic rhinitis and 540 patients with perennial allergic rhinitis were treated with two sprays per nostril of either azelastine hydrochloride 0.15% or placebo once or twice daily. Overall, adverse reactions were more common in the azelastine hydrochloride 0.15% treatment groups (16 to 31%) than in the placebo groups (11 to 24%). Overall, less than 2% of patients discontinued due to adverse reactions and withdrawal due to adverse reactions was similar among the treatment groups.

Table 3 contains adverse reactions reported with frequencies greater than or equal to 2% and more frequently than placebo in patients treated with azelastine hydrochloride 0.15% in the seasonal and perennial allergic rhinitis controlled clinical trials.

Table 3. Adverse Reactions with ≥2% Incidence in Placebo-Controlled Trials of 2 to 4 Weeks’

Duration with Azelastine Hydrochloride 0.15% in Adult and Adolescent Patients With Seasonal or

Perennial Allergic Rhinitis

 | 2 Sprays Twice Daily |  | 2 Sprays Once Daily
 | Azelastine Hydrochloride 0.15%; (N=523) | Vehicle Placebo; (N=523) | Azelastine Hydrochloride 0.15%; (N=1021) | Vehicle Placebo; (N=816)
Bitter Taste | 31 (6%) | 5 (1%) | 38 (4%) | 2 (<1%)
Nasal Discomfort | 18 (3%) | 12 (2%) | 37 (4%) | 7 (1%)
Epistaxis | 5 (1%) | 7 (1%) | 21 (2%) | 14 (2%)
Sneezing | 9 (2%) | 1 (<1%) | 14 (1%) | 0 (0%)

In the above trials, somnolence was reported in <1% of patients treated with azelastine hydrochloride 0.15% (11 of 1544) or vehicle placebo (1 of 1339).

Long-Term (12 Month) Safety Trial:

In the 12 month, open-label, active-controlled, long-term safety trial, 466 patients (12 years of age and older) with perennial allergic rhinitis were treated with azelastine hydrochloride 0.15% two sprays per nostril twice daily and 237 patients were treated with mometasone nasal spray two sprays per nostril once daily. The most frequently reported adverse reactions (>5%) with azelastine hydrochloride 0.15% were bitter taste, headache, sinusitis, and epistaxis. Focused nasal examinations were performed and no nasal ulcerations or septal perforations were observed. In each treatment group, approximately 3% of patients had mild epistaxis. No patients had reports of severe epistaxis. Fifty-four patients (12%) treated with azelastine hydrochloride 0.15% and 17 patients (7%) treated with mometasone nasal spray discontinued from the trial due to adverse events.

6.2 Postmarketing Experience

During the post approval use of azelastine hydrochloride 0.15%, the following adverse reactions have been identified. Because these reactions are reported voluntarily from a population of uncertain size, it is not always possible to reliably estimate their frequency or establish a causal relationship to drug exposure. Adverse reactions reported include: abdominal pain, atrial fibrillation, blurred vision, chest pain, confusion, disturbance or loss of sense of smell and/or taste, dizziness, dyspnea, facial swelling, hypertension, involuntary muscle contractions, nasal burning, nausea, nervousness, palpitations, paresthesia, parosmia, pruritus, rash, sneezing, insomnia, sweet taste, tachycardia, and throat irritation.

Additionally, the following adverse reactions have been identified during the post approval use of the Astelin brand of azelastine hydrochloride 0.1% nasal spray (total daily dose 0.55 mg to 1.1 mg). Because these reactions are reported voluntarily from a population of uncertain size, it is not always possible to reliably estimate their frequency or establish a causal relationship to drug exposure. Adverse reactions reported include the following: anaphylactoid reaction, application site irritation, facial edema, paroxysmal sneezing, tolerance, urinary retention, and xerophthalmia.

7 DRUG INTERACTIONS

7.1 Central Nervous System Depressants

Concurrent use of azelastine hydrochloride nasal spray with alcohol or other central nervous system depressants should be avoided because reductions in alertness and impairment of central nervous system performance may occur [see Warnings and Precautions (5.1)].

7.2 Erythromycin and Ketoconazole

Interaction studies investigating the cardiac effects, as measured by the corrected QT interval (QTc), of concomitantly administered oral azelastine hydrochloride and erythromycin or ketoconazole were conducted. Oral erythromycin (500 mg three times daily for 7 days) had no effect on azelastine pharmacokinetics or QTc based on analyses of serial electrocardiograms. Ketoconazole (200 mg twice daily for 7 days) interfered with the measurement of azelastine plasma concentrations on the analytic HPLC; however, no effects on QTc were observed [see Clinical Pharmacology (12.2) and (12.3)].

7.3 Cimetidine

Cimetidine (400 mg twice daily) increased the mean Cmax and AUC of orally administered azelastine hydrochloride (4 mg twice daily) by approximately 65% [see Clinical Pharmacology (12.3)].

8 USE IN SPECIFIC POPULATIONS

8.1 Pregnancy

Risk Summary

Limited data from postmarketing experience over decades of use with azelastine hydrochloride in pregnant women have not identified any drug associated risks of miscarriage, birth defects, or other adverse maternal or fetal outcomes. In animal reproduction studies, there was no evidence of fetal harm at oral doses approximately 4 times the clinical daily dose. Oral administration of azelastine hydrochloride to pregnant mice, rats, and rabbits, during the period of organogenesis, produced developmental toxicity that included structural abnormalities, decreased embryo-fetal survival, and decreased fetal body weights at doses 180 times and higher than the maximum recommended human daily intranasal dose (MRHDID) of 1.644 mg. However, the relevance of these findings in animals to pregnant women was considered questionable based upon the high animal to human dose multiple.

The estimated background risk of major birth defects and miscarriage for the indicated populations is unknown. All pregnancies have a background risk of birth defect, loss, or other adverse outcomes. In the U.S. general population, the estimated background risk of major birth defects and miscarriage in clinically recognized pregnancies is 2 to 4% and 15 to 20%, respectively.

Data

Animal Data

In an embryo-fetal development study in mice dosed during the period of organogenesis, azelastine hydrochloride caused embryo-fetal death, structural abnormalities (cleft palate; short or absent tail; fused, absent or branched ribs), delayed ossification, and decreased fetal weight at approximately 200 times the maximum recommended human daily intranasal dose (MRHDID) in adults (on a mg/m^2 basis at a maternal oral dose of 68.6 mg/kg/day), which also caused maternal toxicity as evidenced by decreased maternal body weight. Neither fetal nor maternal effects occurred in mice at approximately 9 times the MRHDID in adults (on a mg/m^2 basis at a maternal oral dose of 3 mg/kg/day).

In an embryo-fetal development study in pregnant rats dosed during the period of organogenesis from gestation days 7 to 17, azelastine hydrochloride caused structural abnormalities (oligo-and brachydactylia), delayed ossification, and skeletal variations, in the absence of maternal toxicity, at approximately 180 times the MRHDID in adults (on a mg/m2 basis at a maternal oral dose of 30 mg/kg/day). Azelastine hydrochloride caused embryo-fetal death and decreased fetal weight and severe maternal toxicity at approximately 410 times the MRHDID (on a mg/m^2 basis at a maternal oral dose of 68.6 mg/ kg/day). Neither fetal nor maternal effects occurred at approximately 10 times the MRHDID (on a mg/m^2 basis at a maternal oral dose of 2 mg/kg/day).

In an embryo-fetal development study in pregnant rabbits dosed during the period of organogenesis from gestation days 6 to 18, azelastine hydrochloride caused abortion, delayed ossification and decreased fetal weight and severe maternal toxicity at approximately 360 times the MRHDID in adults (on a mg/m^2 basis at a maternal oral dose of 30 mg/kg/day). Neither fetal nor maternal effects occurred at approximately 4 times the MRHDID (on a mg/m^2 basis at a maternal oral dose of 0.3 mg/kg/day).

In a prenatal and postnatal development study in pregnant rats dosed from late in the gestation period and through the lactation period from gestation day 17 through lactation day 21, azelastine hydrochloride produced no adverse developmental effects on pups at maternal doses up to approximately 180 times the MRHDID (on mg/m^2 basis at a maternal dose of 30 mg/kg/day).

8.2 Lactation

Risk Summary

There are no data on the presence of azelastine hydrochloride in human milk, the effects on the breastfed infant, or the effects on milk production following use of azelastine hydrochloride. Because many drugs are excreted in human milk, caution should be exercised when azelastine hydrochloride is administered to a nursing woman.

The developmental and health benefits of breastfeeding should be considered along with the mother’s clinical need for azelastine hydrochloride and any potential adverse effects on the breastfed infant from azelastine hydrochloride or from the underlying maternal condition.

8.4 Pediatric Use

The safety and effectiveness of azelastine hydrochloride 0.15% have been established for seasonal allergic rhinitis in pediatric patients 6 to 17 years of age and perennial allergic rhinitis in pediatric patients 6 to 17 years of age [see Clinical Studies (14)]. The safety and effectiveness of azelastine hydrochloride 0.15% in pediatric patients below 6 years of age have not been established.

8.5 Geriatric Use

Clinical trials of azelastine hydrochloride did not include sufficient numbers of patients 65 years of age and older to determine whether they respond differently from younger patients. Other reported clinical experience has not identified differences in responses between the elderly and younger patients. In general, dose selection for an elderly patient should be cautious, usually starting at the low end of the dosing range, reflecting the greater frequency of decreased hepatic, renal, or cardiac function, and of concomitant disease or other drug therapy.

10 OVERDOSAGE

There have been no reported overdosages with azelastine hydrochloride nasal spray. Acute overdosage by adults with this dosage form is unlikely to result in clinically significant adverse events, other than increased somnolence, since one 30-mL bottle of azelastine hydrochloride nasal spray, 0.15% contains up to 45 mg of azelastine hydrochloride. Clinical trials in adults with single doses of the oral formulation of azelastine hydrochloride (up to 16 mg) have not resulted in increased incidence of serious adverse events. General supportive measures should be employed if overdosage occurs. There is no known antidote to azelastine hydrochloride. Oral ingestion of antihistamines has the potential to cause serious adverse effects in children. Accordingly, azelastine hydrochloride nasal spray should be kept out of the reach of children.

11 DESCRIPTION

Azelastine Hydrochloride 0.15% Nasal Spray is an antihistamine (H1-receptor antagonist) formulated as a metered-spray solution for intranasal administration.

Azelastine hydrochloride occurs as a white, almost odorless, crystalline powder with a bitter taste. It has a molecular weight of 418.37. It is sparingly soluble in water, methanol, and propylene glycol and slightly soluble in ethanol, octanol, and glycerine. It has a melting point of about 225°C and the pH of a saturated solution is between 5.0 and 5.4. Its chemical name is (±)-1-(2H)-phthalazinone,4-[(4-chlorophenyl) methyl]-2-(hexahydro-1-methyl-1H-azepin-4-yl)-, monohydrochloride. Its molecular formula is C22H24 ClN3 O•HCl with the following chemical structure:

Azelastine Hydrochloride 0.15% Nasal Spray contains 0.15% azelastine hydrochloride in an isotonic aqueous solution containing sorbitol, sucralose, hypromellose, sodium citrate, edetate disodium, benzalkonium chloride (125 mcg/mL), and purified water (pH 6.4). After priming [see Dosage and Administration (2.3)], each metered spray delivers a 0.137 mL mean volume containing 205.5 mcg of azelastine hydrochloride (equivalent to 187.6 mcg of azelastine base). The 30-mL (net weight 30 gm of solution) bottle provides 200 metered sprays.

12 CLINICAL PHARMACOLOGY

12.1 Mechanism of Action

Azelastine hydrochloride, a phthalazinone derivative, exhibits histamine H1-receptor antagonist activity in isolated tissues, animal models, and humans. Azelastine hydrochloride is administered as a racemic mixture with no difference in pharmacologic activity noted between the enantiomers in in vitro studies. The major metabolite, desmethylazelastine, also possesses H1-receptor antagonist activity.

12.2 Pharmacodynamics

Cardiac Effects:

In a placebo-controlled trial (95 patients with allergic rhinitis), there was no evidence of an effect of azelastine hydrochloride nasal spray (2 sprays per nostril twice daily for 56 days) on cardiac repolarization as represented by the corrected QT interval (QTc) of the electrocardiogram. Following multiple dose oral administration of azelastine 4 mg or 8 mg twice daily, the mean change in QTc was 7.2 msec and 3.6 msec, respectively.

Interaction studies investigating the cardiac repolarization effects of concomitantly administered oral azelastine hydrochloride and erythromycin or ketoconazole were conducted. Oral erythromycin had no effect on azelastine pharmacokinetics or QTc based on analysis of serial electrocardiograms. Ketoconazole interfered with the measurement of azelastine plasma levels; however, no effects on QTc were observed [see Drug Interactions (7.2)].

12.3 Pharmacokinetics

Absorption:

After intranasal administration of 2 sprays per nostril (822 mcg total dose) of azelastine hydrochloride 0.15%, the mean azelastine peak plasma concentration (Cmax) is 409 pg/mL, the mean extent of systemic exposure (AUC) is 9312 pg•hr/mL and the median time to reach Cmax (tmax) is 4 hours. The systemic bioavailability of azelastine hydrochloride is approximately 40% after intranasal administration.

Distribution:

Based on intravenous and oral administration, the steady-state volume of distribution of azelastine is 14.5 L/kg. In vitro studies with human plasma indicate that the plasma protein binding of azelastine and its metabolite, desmethylazelastine, are approximately 88% and 97%, respectively.

Metabolism:

Azelastine is oxidatively metabolized to the principal active metabolite, desmethylazelastine, by the cytochrome P450 enzyme system. The specific P450 isoforms responsible for the biotransformation of azelastine have not been identified. After a single-dose, intranasal administration of azelastine hydrochloride 0.15% (822 mcg total dose), the mean desmethylazelastine Cmax is 38 pg/mL, the AUC is 3824 pg•hr/mL and the median tmax is 24 hours. After intranasal dosing of azelastine to steady-state, plasma concentrations of desmethylazelastine range from 20 to 50% of azelastine concentrations.

Elimination:

Following intranasal administration of azelastine hydrochloride 0.15%, the elimination half-life of azelastine is 25 hours while that of desmethylazelastine is 57 hours. Approximately 75% of an oral dose of radiolabeled azelastine hydrochloride was excreted in the feces with less than 10% as unchanged azelastine.

Special Populations:

Hepatic Impairment: Following oral administration, pharmacokinetic parameters were not influenced by hepatic impairment.

Renal Impairment: Based on oral, single-dose studies, renal insufficiency (creatinine clearance <50 mL/min) resulted in a 70 to 75% higher Cmax and AUC compared to healthy subjects. Time to maximum concentration was unchanged.

Age: Following oral administration, pharmacokinetic parameters were not influenced by age.

Gender: Following oral administration, pharmacokinetic parameters were not influenced by gender.

Race: The effect of race has not been evaluated.

Drug-Drug Interactions:

Erythromycin: Co-administration of orally administered azelastine (4 mg twice daily) with erythromycin (500 mg three times daily for 7 days) resulted in Cmax of 5.36 ± 2.6 ng/mL and AUC of 49.7 ± 24 ng•h/mL for azelastine, whereas, administration of azelastine alone resulted in Cmax of 5.57 ± 2.7 ng/mL and AUC of 48.4 ± 24 ng•h/mL for azelastine [see Drug Interactions (7.2)].

Cimetidine and Ranitidine: In a multiple-dose, steady-state drug interaction trial in healthy subjects, cimetidine (400 mg twice daily) increased orally administered mean azelastine (4 mg twice daily) concentrations by approximately 65%. Co-administration of orally administered azelastine (4 mg twice daily) with ranitidine hydrochloride (150 mg twice daily) resulted in Cmax of 8.89 ± 3.28 ng/mL and AUC of 88.22 ± 40.43 ng•h/mL for azelastine, whereas, administration of azelastine alone resulted in Cmax of 7.83 ± 4.06 ng/mL and AUC of 80.09 ± 43.55 ng•h/mL for azelastine [see Drug Interactions (7.3)].

Theophylline: No significant pharmacokinetic interaction was observed with the co-administration of an oral 4 mg dose of azelastine hydrochloride twice daily and theophylline 300 mg or 400 mg twice daily.

13 NONCLINICAL TOXICOLOGY

13.1 Carcinogenesis, Mutagenesis, Impairment of Fertility

Two-year carcinogenicity studies in Crl:CD(SD)BR rats and NMRI mice were conducted to assess the carcinogenic potential of azelastine hydrochloride. No evidence of tumorigenicity was observed in rats at doses up to 30 mg/kg day (approximately 180 and 160 times the MRHDID for adults and children, respectively, on a mg/m^2 basis). No evidence for tumorigenicity was observed in mice at doses up to 25 mg/kg (approximately 75 and 65 times the MRHDID for adults and children, respectively, on a mg/m^2 basis).

Azelastine hydrochloride showed no genotoxic effects in the Ames test, DNA repair test, mouse lymphoma forward mutation assay, mouse micronucleus test, or chromosomal aberration test in rat bone marrow.

There were no effects on male or female fertility and reproductive performance in male and female rats at oral doses up to 30 mg/kg (approximately 180 times the MRHDID in adults on a mg/m^2 basis). At 68.6 mg/kg (approximately 410 times the MRHDID on a mg/m^2 basis), the duration of estrous cycles was prolonged and copulatory activity and the number of pregnancies were decreased. The numbers of corpora lutea and implantations were decreased; however, preimplantation loss was not increased.

14 CLINICAL STUDIES

14.1 Seasonal Allergic Rhinitis

Azelastine Hydrochloride 0.15% Nasal Spray

The efficacy and safety of azelastine hydrochloride 0.15% in seasonal allergic rhinitis was evaluated in five randomized, multicenter, double-blind, placebo-controlled clinical trials in 2499 adult and adolescent patients 12 years and older with symptoms of seasonal allergic rhinitis (Trials 2, 3, 4, 5, and 6). The population of the trials was 12 to 83 years of age (64% female, 36% male, 81% white, 12% black, <2% Asian, 5% other; 23% Hispanic, 77% non-Hispanic). Assessment of efficacy was based on the rTNSS, iTNSS as described above, and other supportive secondary efficacy variables. The primary efficacy endpoint was the mean change from baseline in rTNSS over 2 weeks.

Two 2-week seasonal allergic rhinitis trials evaluated the efficacy of azelastine hydrochloride nasal spray, 0.15% dosed at 2 sprays twice daily. The first trial (Trial 2) compared the efficacy of azelastine hydrochloride 0.15% and Astelin (azelastine hydrochloride) Nasal Spray to vehicle placebo. The other trial (Trial 3) compared the efficacy of azelastine hydrochloride 0.15% to vehicle placebo. In these two trials, azelastine hydrochloride 0.15% demonstrated greater decreases in rTNSS than placebo and the differences were statistically significant (Table 4).

Three 2-week seasonal allergic rhinitis trials evaluated the efficacy of azelastine hydrochloride, 0.15% dosed at 2 sprays once daily compared to the vehicle placebo. Trial 4 demonstrated a greater decrease in rTNSS than placebo and the difference was statistically significant (Table 4). Trial 5 and Trial 6 were conducted in patients with Texas mountain cedar allergy. In Trial 5 and Trial 6, azelastine hydrochloride 0.15% demonstrated a greater decrease in rTNSS than placebo and the differences were statistically significant (Trials 5 and 6; Table 4). Instantaneous TNSS results for the once daily dosing regimen of azelastine hydrochloride 0.15% are shown in Table 5. In Trials 5 and 6, azelastine hydrochloride 0.15% demonstrated a greater decrease in iTNSS than placebo and the differences were statistically significant.

Table 4. Mean Change from Baseline in Reflective TNSS over 2 Weeks* in Adults and Children ≥ 12 years with Seasonal Allergic Rhinitis

 | Treatment; (sprays per; nostril) | n | Baseline; LS Mean | Change; from; Baseline | Difference From Placebo; LS Mean 95% CI P value
Trial 2
Two sprays twice daily | Azelastine Hydrochloride 0.15%; Astelin Nasal Spray; Vehicle Placebo | 153; 153; 153 | 18.2; 17.9; 18.1 | -4.3; -3.9; -3.0 | -1.2; -0.9 | -2.1, -0.3; -1.8, 0.1 | 0.01; 0.07
Trial 3
Two sprays twice daily | Azelastine Hydrochloride 0.15%; Vehicle Placebo | 177; 177 | 17.7; 17.7 | -5.1; -2.1 | -3.0 | -3.9, -2.1 | <0.001
Trial 4
Two sprays once daily | Azelastine Hydrochloride 0.15%; Vehicle Placebo | 238; 242 | 17.4; 17.4 | -3.4; -2.4 | -1.0 | -1.7, -0.3 | 0.008
Trial 5
Two sprays once daily | Azelastine Hydrochloride 0.15%; Vehicle Placebo | 266; 266 | 18.5; 18.0 | -3.3; -1.9 | -1.4 | -2.1, -0.8 | <0.001
Trial 6
Two sprays once daily | Azelastine Hydrochloride 0.15%; Vehicle Placebo | 251; 254 | 18.5; 18.8 | -3.4; -2.0 | -1.4 | -2.1, -0.7 | <0.001
*Sum of AM and PM rTNSS for each day (Maximum score=24) and averaged over the 14 day treatment period

Table 5. Mean Change from Baseline AM Instantaneous TNSS over 2 Weeks* in Adults and Children ≥ 12 years with Seasonal Allergic Rhinitis

 | Treatment; (sprays per nostril once daily) | n | Baseline; LS Mean | Change; from; Baseline | Difference From Placebo; LS 95% CI P value; Mean
Trial 4
Two sprays once daily | Azelastine Hydrochloride 0.15%; Vehicle Placebo | 238; 242 | 8.1; 8.3 | -1.3; -1.1 | -0.2 | -0.6, 0.1 | 0.15
Trial 5
Two sprays once daily | Azelastine Hydrochloride 0.15%; Vehicle Placebo | 266; 266 | 8.7; 8.3 | -1.4; -0.7 | -0.7 | -1.0, -0.4 | <0.001
Trial 6
Two sprays once daily | Azelastine Hydrochloride 0.15%; Vehicle Placebo | 251; 254 | 8.9; 8.9 | -1.4; -0.8 | -0.6 | -0.9, -0.3 | <0.001
*AM iTNSS for each day (Maximum score=12) and averaged over the 14 day treatment period

Azelastine hydrochloride 0.15% at a dose of 1 spray twice daily was not studied. The azelastine hydrochloride 0.15% 1 spray twice daily dosing regimen is supported by previous findings of efficacy for Astelin (azelastine hydrochloride) Nasal Spray and a favorable comparison of azelastine hydrochloride 0.15% to Astelin Nasal Spray (Table 4).

The efficacy and safety of azelastine hydrochloride 0.15% in children 6 to 11 years of age with seasonal allergic rhinitis was evaluated in a clinical study that enrolled pediatric patients with perennial allergic rhinitis, with or without concomitant seasonal allergic rhinitis (described below in Section 14.2).

14.2 Perennial Allergic Rhinitis

Azelastine Hydrochloride 0.15% Nasal Spray

The efficacy and safety of azelastine hydrochloride 0.15% in perennial allergic rhinitis was evaluated in one randomized, multicenter, double-blind, placebo-controlled clinical trial in 578 adult and adolescent patients 12 years and older with symptoms of perennial allergic rhinitis. The population of the trial was 12 to 84 years of age (68% female, 32% male; 85% white, 11% black, 1% Asian, 3% other; 17% Hispanic, 83% non-Hispanic).

Assessment of efficacy was based on the 12-hour reflective total nasal symptom score (rTNSS) assessed daily in the morning and evening, the instantaneous total nasal symptom score (iTNSS), and other supportive secondary efficacy variables. The primary efficacy endpoint was the mean change from baseline rTNSS over 4 weeks. The one 4-week perennial allergic rhinitis trial evaluated the efficacy of azelastine hydrochloride 0.15%, and vehicle placebo dosed at 2 sprays per nostril twice daily. In this trial, azelastine hydrochloride 0.15% demonstrated a greater decrease in rTNSS than placebo and the difference was statistically significant (Table 6).

Table 6. Mean Change from Baseline in Reflective TNSS over 4 Weeks* in Adults and Children ≥ 12 years with Perennial Allergic Rhinitis

 | Treatment (sprays per; nostril twice daily) | n | Baseline; LS Mean | Change; from; Baseline | Difference From Placebo; LS 95% CI P value; Mean
Two sprays twice daily | Azelastine Hydrochloride 0.15%; Vehicle Placebo | 192; 192 | 15.8; 14.7 | -4.0; -3.1 | -0.9 | -1.7, -0.1 | 0.03
*Sum of AM and PM rTNSS for each day (Maximum score=24) and averaged over the 28 day treatment period

The efficacy and safety of azelastine hydrochloride 0.15% in pediatric patients 6 to 11 years of age with perennial allergic rhinitis, with or without concomitant seasonal allergic rhinitis, was evaluated in a randomized, double-blind, placebo-controlled clinical trial in 486 patients. All patients received one spray per nostril twice daily. The study population was 58% males and 42% females; 78% white, 13% black, 3% Asian, and 6% other.

Assessment of efficacy was based on the 12-hour reflective total nasal symptom score (rTNSS) assessed daily in the morning and evening. The primary efficacy endpoint was the mean change from baseline rTNSS over 4 weeks (Table 7). Both active treatments demonstrated statistically significant decreases in rTNSS compared to placebo. There was no statistically significant difference between the two active-treatment groups. There was also no difference in treatment effect between patients with perennial allergic rhinitis only compared to those with perennial allergic rhinitis and concomitant seasonal allergic rhinitis.

Table 7. Mean Change from Baseline in Reflective TNSS over 4 Weeks* in Children 6 to 11 years with Perennial Allergic Rhinitis

 | Treatment (sprays per nostril twice daily) | n | Baseline; LS Mean | Change from; Baseline | Difference From Placebo; LS 95% CI P value; Mean
One spray twice daily | Azelastine Hydrochloride 0.15%; Vehicle Placebo | 159; 161 | 16.6; 16.1 | -3.5 | -1.0 | -1.7, -0.3 | 0.005
*Sum of AM and PM rTNSS for each day (Maximum score=24) and averaged over the 28 day treatment period

The efficacy of azelastine hydrochloride nasal spray, 0.15%, in children 6 months to 5 years of age with allergic rhinitis was explored in a clinical study (described above in Section 14.1).

16 HOW SUPPLIED/STORAGE AND HANDLING

Azelastine Hydrochloride 0.15% Nasal Spray is supplied as a 30-mL package (NDC 50383-942-30) delivering 200 metered sprays in a high-density polyethylene (HDPE) bottle fitted with a metered-dose spray pump unit. The spray pump unit consists of a nasal spray pump fitted with a white safety clip and a clear plastic dust cover. The net content of the bottle is 30 mL (net weight 30 gm of solution). The 30-mL bottle contains 45 mg (1.5 mg/mL) of azelastine hydrochloride. After priming [see Dosage and Administration (2.3)], each spray delivers a fine mist containing a mean volume of 0.137 mL solution containing 205.5 mcg of azelastine hydrochloride. The correct amount of medication in each spray cannot be assured before the initial priming and after 200 sprays for the 30-mL bottle have been used, even though the bottle is not completely empty. The bottle should be discarded after 200 sprays have been used.

Azelastine Hydrochloride Nasal Spray should not be used after the expiration date “EXP” printed on the medicine label and carton.

Storage

Store upright at controlled room temperature 20° to 25°C (68° to 77°F). Protect from freezing.

17 PATIENT COUNSELING INFORMATION

See FDA-approved patient labeling (Patient Information and Instructions for Use).

Activities Requiring Mental Alertness

Somnolence has been reported in some patients taking azelastine hydrochloride nasal spray. Caution patients against engaging in hazardous occupations requiring complete mental alertness and motor coordination such as driving or operating machinery after administration of azelastine hydrochloride nasal spray [see Warnings and Precautions (5.1)].

Concurrent Use of Alcohol and other Central Nervous System Depressants

Avoid concurrent use of azelastine hydrochloride nasal spray with alcohol or other central nervous system depressants because additional reductions in alertness and additional impairment of central nervous system performance may occur [see Warnings and Precautions (5.1)].

Common Adverse Reactions

Inform patients that the treatment with azelastine hydrochloride nasal spray may lead to adverse reactions, most common of which include pyrexia, dysgeusia, nasal discomfort, epistaxis, headache, sneezing, fatigue, somnolence, upper respiratory infection, cough, rhinalgia, vomiting, otitis media, contact dermatitis, and oropharyngeal pain [see Adverse Reactions (6.1)].

Priming

Instruct patients to prime the pump before initial use and when azelastine hydrochloride nasal spray has not been used for 3 or more days [see Dosage and Administration (2.3)].

Keep Spray Out of Eyes

Instruct patients to avoid spraying azelastine hydrochloride nasal spray into their eyes.

Keep Out of Children’s Reach

Instruct patients to keep azelastine hydrochloride nasal spray out of the reach of children. If a child accidentally ingests azelastine hydrochloride nasal spray, seek medical help or call a poison control center immediately.

Manufactured by:

Hi-Tech Pharmacal Co., Inc.

Amityville, NY 11701

Rev.942:01 01/20

PATIENT INFORMATION

Azelastine Hydrochloride Nasal Spray, 0.15%

(a zel’ as teen)

Important: For use in your nose only.

What is Azelastine Hydrochloride Nasal Spray?

- Azelastine Hydrochloride Nasal Spray is a prescription medicine used to treat symptoms of seasonal allergic rhinitis in patients 6 years of age and older and year-round allergic rhinitis in people age 6 years and older.
- Azelastine Hydrochloride Nasal Spray may help to reduce your nasal symptoms including stuffy nose, runny nose, itching and sneezing.

It is not known if Azelastine Hydrochloride Nasal Spray is safe and effective in children under 6 years of age.

What should I tell my healthcare provider before using Azelastine Hydrochloride Nasal Spray?

Before using Azelastine Hydrochloride Nasal Spray, tell your healthcare provider if you are:

- allergic to any of the ingredients in Azelastine Hydrochloride Nasal Spray. See the end of this leaflet for a complete list of ingredients in Azelastine Hydrochloride Nasal Spray.
- pregnant, or plan to become pregnant.
- breastfeeding, or plan to breastfeed. It is not known if Azelastine Hydrochloride passes into your breast milk. You and your healthcare provider should decide if you will use Azelastine Hydrochloride Nasal Spray if you plan to breastfeed.

Tell your healthcare provider about all the medicines you take, including prescription and over-the-counter medicines, vitamins, and herbal supplements. Azelastine Hydrochloride Nasal Spray and other medicines may affect each other, causing side effects.

How should I use Azelastine Hydrochloride Nasal Spray?

- Read the Instructions for Use at the end of this leaflet for information about the right way to use AzelastineHydrochloride Nasal Spray.
- An adult should help a young child use Azelastine Hydrochloride Nasal Spray.
- Spray Azelastine Hydrochloride Nasal Spray in your nose only. Do not spray it into your eyes or mouth.
- Use Azelastine Hydrochloride Nasal Spray exactly as your healthcare provider tells you to use it.
- Do not use more than your healthcare provider tells you.
- Throw away your Azelastine Hydrochloride Nasal Spray, 0.15% bottle after using 200 sprays. Even though the bottle may not be completely empty, you may not get the correct dose of medicine.
- If you use too much or a child accidentally swallows Azelastine Hydrochloride, call your healthcare provider or go to the nearest hospital emergency room right away.

What should I avoid while using Azelastine Hydrochloride Nasal Spray?

Azelastine Hydrochloride Nasal Spray can cause sleepiness:

- Do not drive, operate machinery, or do other dangerous activities until you know how Azelastine Hydrochloride Nasal Spray affects you.
- Do not drink alcohol or take other medicines that may cause you to feel sleepy while using Azelastine Hydrochloride Nasal Spray. It may make your sleepiness worse.

What are the possible side effects of Azelastine Hydrochloride Nasal Spray?

The most common side effects of Azelastine Hydrochloride Nasal Spray include:

- fever
- unusual taste
- nose pain or discomfort
- nosebleeds
- headache
- sneezing
- fatigue
- sleepiness
- upper respiratory tract infections
- cough
- vomiting
- middle ear infection
- skin rash
- sore throat

Tell your healthcare provider if you have any side effect that bothers you or that does not go away.

These are not all of the possible side effects of Azelastine Hydrochloride Nasal Spray. For more information, ask your healthcare provider or pharmacist.

Call your doctor for medical advice about side effects. You may report side effects to FDA at 1-800-FDA-1088.

How should I store Azelastine Hydrochloride Nasal Spray?

- Keep Azelastine Hydrochloride Nasal Spray upright at 68°F to 77°F (20°C to 25°C).
- Do not freeze Azelastine Hydrochloride Nasal Spray.
- Do not use Azelastine Hydrochloride Nasal Spray after the expiration date “EXP” on the medicine label and box.

Keep Azelastine Hydrochloride Nasal Spray and all medicines out of reach of children.

General information about the safe and effective use of Azelastine Hydrochloride Nasal Spray.

Medicines are sometimes prescribed for conditions other than those listed in a Patient Information leaflet. Do not use Azelastine Hydrochloride Nasal Spray for a condition for which it was not prescribed. Do not give Azelastine Hydrochloride Nasal Spray to other people, even if they have the same symptoms that you have. It may harm them.

This Patient Information leaflet summarizes the most important information about Azelastine Hydrochloride Nasal Spray. If you would like more information, talk with your healthcare provider. You can ask your pharmacist or healthcare provider for information about Azelastine Hydrochloride Nasal Spray that is written for health professionals.

For more information, call 1-800-262-9010.

What are the ingredients in Azelastine Hydrochloride Nasal Spray?

Active ingredient: azelastine hydrochloride

Inactive ingredients: sorbitol, sucralose, hypromellose, sodium citrate, edetate disodium, benzalkonium chloride, and purified water.

Manufactured by:

Hi-Tech Pharmacal Co., Inc.

Amityville, NY 11701

Rev.942:01 01/20

Instructions for Use

Azelastine Hydrochloride Nasal Spray, 0.15%

(a zel’ as teen)

Important: For use in your nose only.

For the correct dose of medicine:

- Keep your head tilted downward when spraying into your nostril.
- Change nostrils each time you use the spray.
- Breathe gently and do not tip your head back after using the spray. This will keep the medicine from running down into your throat. You may get a bitter taste in your mouth.

Figure A identifies the parts of your Azelastine Hydrochloride Nasal Spray pump

Before you use Azelastine Hydrochloride Nasal Spray for the first time, you will need to prime the bottle.

For use in young children: An adult should help a young child use Azelastine Hydrochloride Nasal Spray. (See “Using your Azelastine Hydrochloride Nasal Spray” Steps 1 through 8).

Priming your Azelastine Hydrochloride Nasal Spray

Remove the clear dust cover over the tip of the bottle and the white safety clip just under the “shoulders” of the bottle (See Figure B).

- Hold the bottle upright with 2 fingers on the shoulders of the spray pump unit and put your thumb on the bottom of the bottle. Press upward with your thumb and release for the pumping action. Repeat this until you see a fine mist (See Figure C).
- To get a fine mist you must pump the spray fast and use firm pressure against the bottom of the bottle. If you see a stream of liquid, the pump is not working correctly and you may have nasal discomfort.
- This should happen in 6 sprays or less.

Now your pump is primed and ready to use.

- Do not use Azelastine Hydrochloride Nasal Spray unless you see a fine mist after you do the priming sprays. If you do not see a fine mist, clean the tip of the spray nozzle. See the “Cleaning the Spray Tip of your Azelastine Hydrochloride Nasal Spray” section below.
- If you do not use Azelastine Hydrochloride Nasal Spray for 3 or more days, you will need to prime the pump with 2 sprays or until you see a fine mist.

Using your Azelastine Hydrochloride Nasal Spray

For use in young children: An adult should help a young child use Azelastine Hydrochloride Nasal Spray (See Steps 1 through 8).

Step 1. Blow your nose to clear your nostrils.

Step 2. Keep your head tilted downward toward your toes.

Step 3. Place the spray tip about ¼ inch to ½ inch into 1 nostril. Hold bottle upright and aim the spray tip toward the back of your nose (See Figure D).

Step 4. Close your other nostril with a finger. Press the pump 1 time and sniff gently at the same time, keeping your head tilted forward and down (See Figure E).

Step 5. Repeat Step 3 and Step 4 in your other nostril.

Step 6. If your healthcare provider tells you to use 2 sprays in each nostril, repeat Steps 2 through 4 above for the second spray in each nostril.

Step 7. Breathe in gently, and do not tilt your head back after using Azelastine Hydrochloride Nasal Spray. This will help to keep the medicine from going into your throat.

Step 8. When you finish using your Azelastine Hydrochloride Nasal Spray, wipe the spray tip with a clean tissue or cloth. Put the safety clip and dust cover back on the bottle.

Cleaning the Spray Tip of your Azelastine Hydrochloride Nasal Spray

- If the spray tip opening is clogged, do not use a pin or pointed object to unclog the tip. Unscrew the spray pump unit from the bottle by turning it to the left (counter-clockwise) (See Figure F).
- Soak only the spray pump unit in warm water. Squirt the spray unit several times while holding it under water. Use the pumping action to clear the opening in the tip (See Figure G).

- Let the spray pump unit air dry. Make sure it is dry before you put it back onto the bottle.
- Put the spray pump unit back into the open bottle and tighten it by turning clockwise (to the right).
- To keep the medicine from leaking out, use firm pressure when you put the pump back onto the bottle.
- After cleaning, follow the instructions for priming.

This Patient Information and Instructions for Use has been approved by the U.S. Food and Drug Administration.

Manufactured by:

Hi-Tech Pharmacal Co., Inc.

Amityville, NY 11701

Rev.942:01 01/20

Package/Label Display Panel

AKORN

NDC 50383-942-30

Azelastine Hydrochloride Nasal Spray, 0.15%

205.5 mcg per Spray

FOR INTRANASAL USE ONLY

DO NOT SPRAY IN EYES

Rx only

30 mL